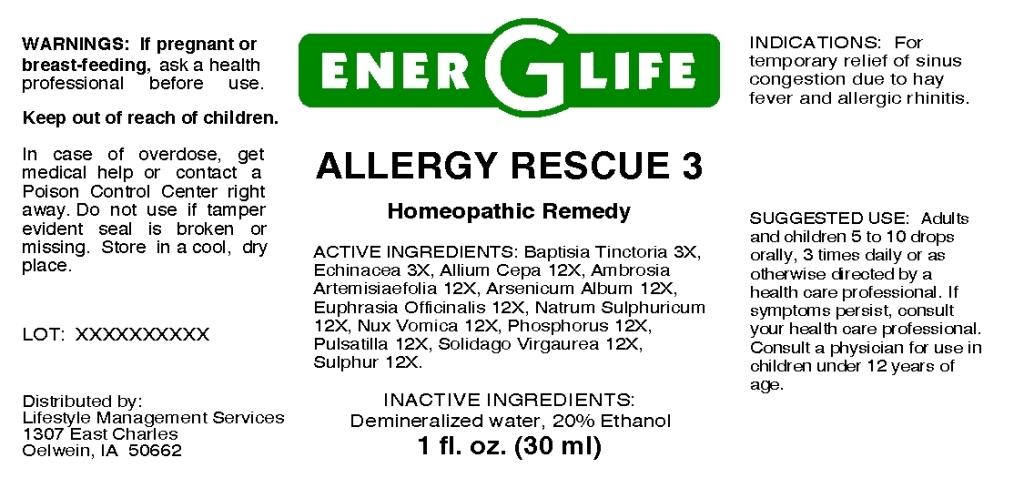 DRUG LABEL: Allergy Rescue
NDC: 57520-0653 | Form: LIQUID
Manufacturer: Apotheca Company
Category: homeopathic | Type: HUMAN OTC DRUG LABEL
Date: 20110331

ACTIVE INGREDIENTS: BAPTISIA TINCTORIA ROOT 3 [hp_X]/1 mL; ECHINACEA 3 [hp_X]/1 mL; ONION 12 [hp_X]/1 mL; AMBROSIA ARTEMISIIFOLIA 12 [hp_X]/1 mL; ARSENIC TRIOXIDE 12 [hp_X]/1 mL; EUPHRASIA STRICTA 12 [hp_X]/1 mL; SODIUM SULFATE 12 [hp_X]/1 mL; STRYCHNOS NUX-VOMICA SEED 12 [hp_X]/1 mL; PHOSPHORUS 12 [hp_X]/1 mL; PULSATILLA VULGARIS 12 [hp_X]/1 mL; SOLIDAGO VIRGAUREA FLOWERING TOP 12 [hp_X]/1 mL; SULFUR 12 [hp_X]/1 mL
INACTIVE INGREDIENTS: WATER; ALCOHOL

Allergy Rescue 3

ACTIVE INGREDIENT

ACTIVE INGREDIENTS: Baptisia tinctoria 3X, Echinacea 3X, Allium cepa 12X, Ambrosia artemisiaefolia 12X, Arsenicum album 12X, Euphrasia officinalis 12X, Natrum sulphuricum 12X, Nux vomica 12X, Phosphorus 12X, Pulsatilla 12X, Solidago virgaurea 12X, Sulphur 12X.

PURPOSE

INDICATIONS: For temporary relief of sinus congestion due to hay fever and allergic rhinitis.

WARNINGS

WARNINGS: If pregnant or breast-feeding, ask a health professional before use.

Keep out of reach of children. In case of overdose, get medical help or contact a Poison Control Center right away.

Do not use if tamper evident seal is broken or missing. Store in a cool, dry place.

DOSAGE AND ADMINISTRATION

SUGGESTED USE: Adults and children 5 to 10 drops orally, 3 times daily or as otherwise directed by a health care professional. If symptoms persist, consult your health care professional. Consult a physician for use in children under 12 years of age.

INACTIVE INGREDIENTS: Demineralized water, 20% Ethanol.

KEEP OUT OF REACH OF CHILDREN. In case of overdose, get medical help or contact a Poison Control Center right away.

INDICATIONS AND USAGE

INDICATIONS: For temporary relief of sinus congestion due to hay fever and allergic rhinitis.

QUESTIONS

Distributed by:

Lifestyle Management Services

1307 East Charles

Oelwein, IA 50662

PACKAGE LABEL

ENER G LIFE

ALLERGY RESCUE 3

Homeopathic Remedy

1 fl. oz. (30 ml)